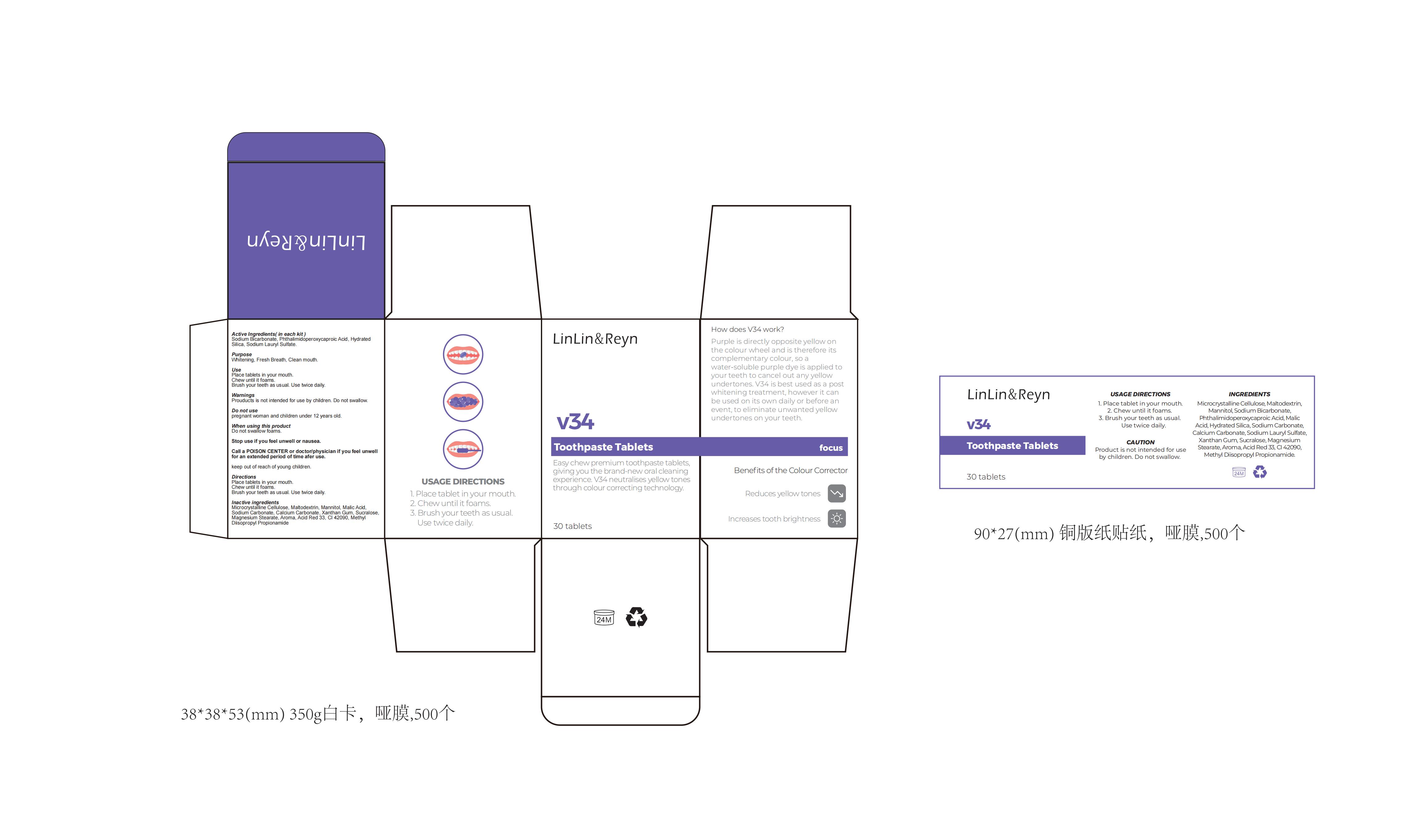 DRUG LABEL: V34 Toothpaste. Tablets.
NDC: 83812-005 | Form: TABLET
Manufacturer: LLRN PERSONAL CARE(SHENZHEN)CO., LTD
Category: otc | Type: HUMAN OTC DRUG LABEL
Date: 20231124

ACTIVE INGREDIENTS: PHTHALIMIDOPEROXYCAPROIC ACID 6 g/100 1; SODIUM BICARBONATE 7 g/100 1; HYDRATED SILICA 5 g/100 1
INACTIVE INGREDIENTS: XANTHAN GUM; SUCRALOSE; FD&C BLUE NO. 1; METHYL DIISOPROPYL PROPIONAMIDE; MICROCRYSTALLINE CELLULOSE; CALCIUM CARBONATE; MALTODEXTRIN; MANNITOL; D&C RED NO. 33; AROMADENDRIN; SODIUM CARBONATE; MALIC ACID; MAGNESIUM STEARATE

Active Ingredient

Sodium Bicarbonate 7%

Phthalimidoperoxycaproic Acid 6%

Hydrated Silica 5%

Purpose

Whitening, Fresh Breath, Clean mouth

Use

Place tablets in your mouth.
Chew until it foams.
Brush your teeth as usual. Use twice daily.

Warnings

Prouducts is not intended for use by children.
Do not swallow.

Do not use

Pregnant woman and children under 12 years old.

When Using

Do not swallow foams.

Stop Use

Stop use if you feel unwell or nausea.

Ask Doctor

Call a POISON CENTER or doctor/physician if you feel unwell for an extended period of time afer use.

Keep Oot Of Reach Of Children

Keep Out Of Reach Of Children

Directions

Place tablets in your mouth.
Chew until it foams.
Brush your teeth as usual. Use twice daily.

Inactive ingredients

Microcrystalline Cellulose, Maltodextrin, Mannitol, Malic Acid, Sodium Carbonate, Calcium Carbonate, Xanthan Gum, Sucralose, Magnesium Stearate, Aroma, Acid Red 33, CI 42090, Methyl Diisopropyl Propionamide